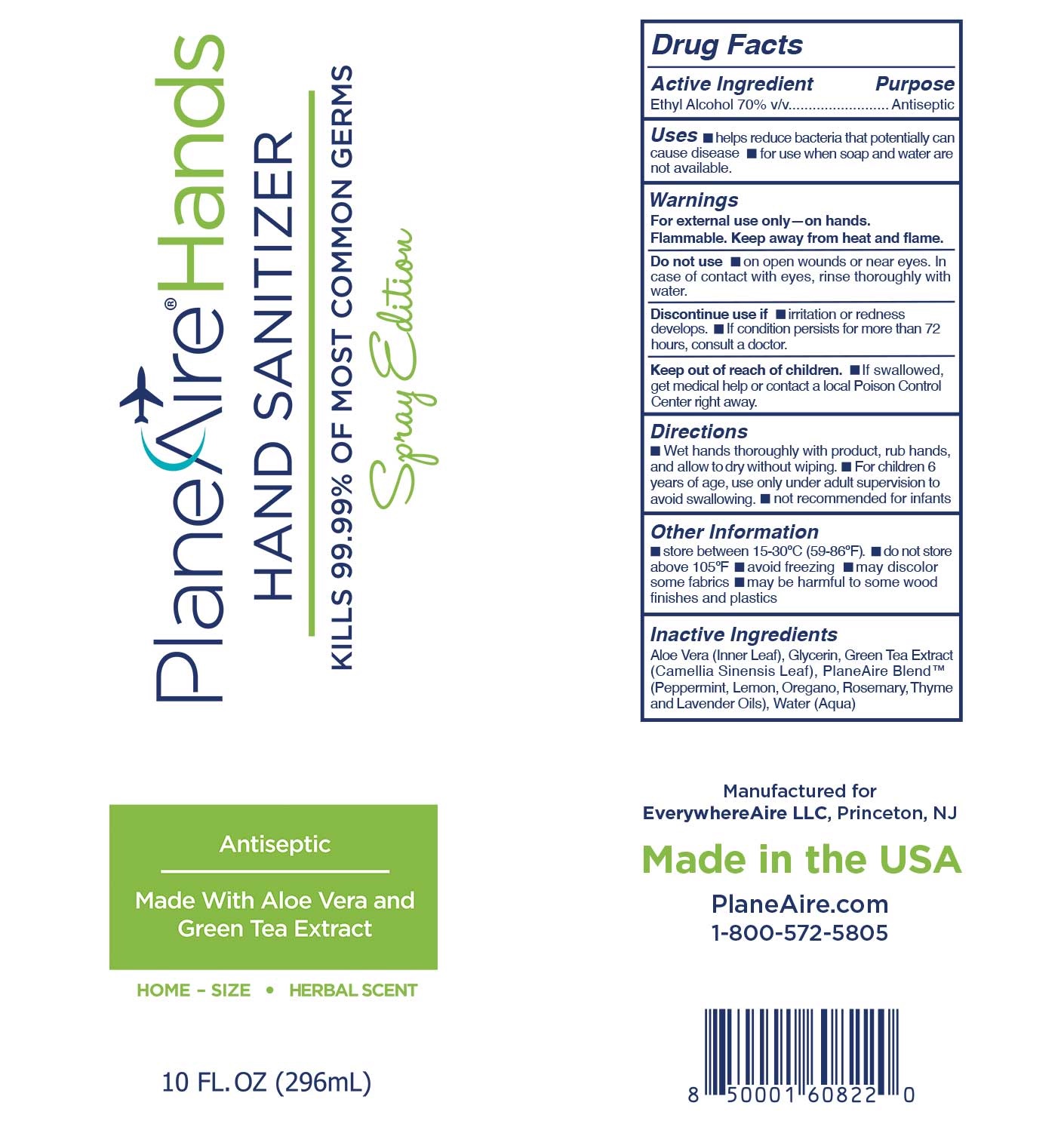 DRUG LABEL: PlaneAire Hands hand sanitizer
NDC: 80335-105 | Form: SPRAY
Manufacturer: EverywhereAire LLC
Category: otc | Type: HUMAN OTC DRUG LABEL
Date: 20231220

ACTIVE INGREDIENTS: ALCOHOL 70 mL/100 mL
INACTIVE INGREDIENTS: ROSEMARY OIL; GLYCERIN; LEMON OIL; WATER; OREGANO LEAF OIL; ALOE VERA LEAF POLYSACCHARIDES; PEPPERMINT OIL; GREEN TEA LEAF; LAVENDER OIL; CARBOMER 980; THYME OIL

PlaneAire Hands Spray edition Hand Sanitizer Herbal 10 oz.

Active Ingredient(s)

Ethyl alcohol 70% v/v.

Purpose

Antiseptic

Use

helps reduce bacteria that potentially can cause disease. For use when soap and water are not available.

Warnings

For external use only- on hands. Flammable. Keep away from heat or flame

Do not use

- on open skin wounds or near eyes. In case of contact with eyes, rinse thoroughly with water

When using this product keep out of eyes. In case of contact with eyes, rinse thoroughly with water.
Stop use if irritation or redness develops. If condition persists for more than 72 hours, consult a doctor.
Keep out of reach of children. If swallowed, get medical help or contact a local Poison Control Center right away.

Stop use if irritation or redness develops. If condition persists for more than 72 hours, consult a doctor.

Keep out of reach of children. If swallowed, get medical help or contact a Poison Control Center right away.

Directions

- Wet hands thoroughly with product , rub hands, and allow to dry without wiping
- For children under 6 years of age, use only under adult supervision to avoid swallowing
- not recommended for infants

Uses Dosage and Administration

- Uses
- helps reduce bacteria that potentially can cause disease. For use when soap and water are not available.
- Dosage and administration
- Wet hands thoroughly with product , rub hands, and allow to dry without wiping
- For children under 6 years of age, use only under adult supervision to avoid swallowing
- not recommended for infants

Other information

- Store between 15-30C (59-86F)
- do not store above 105F
- avoid freezing
- may discolor some fabrics
- may be harmful to some wood finishes and plastics

Inactive ingredients

Aloe vera (inner leaf), Glycerin, Green tea extract (Camelia Sinensis leaf), PlaneAire blend (Peppermint, Lemon, Oregano, Rosemary, Thyme, and Lavender oils), Water